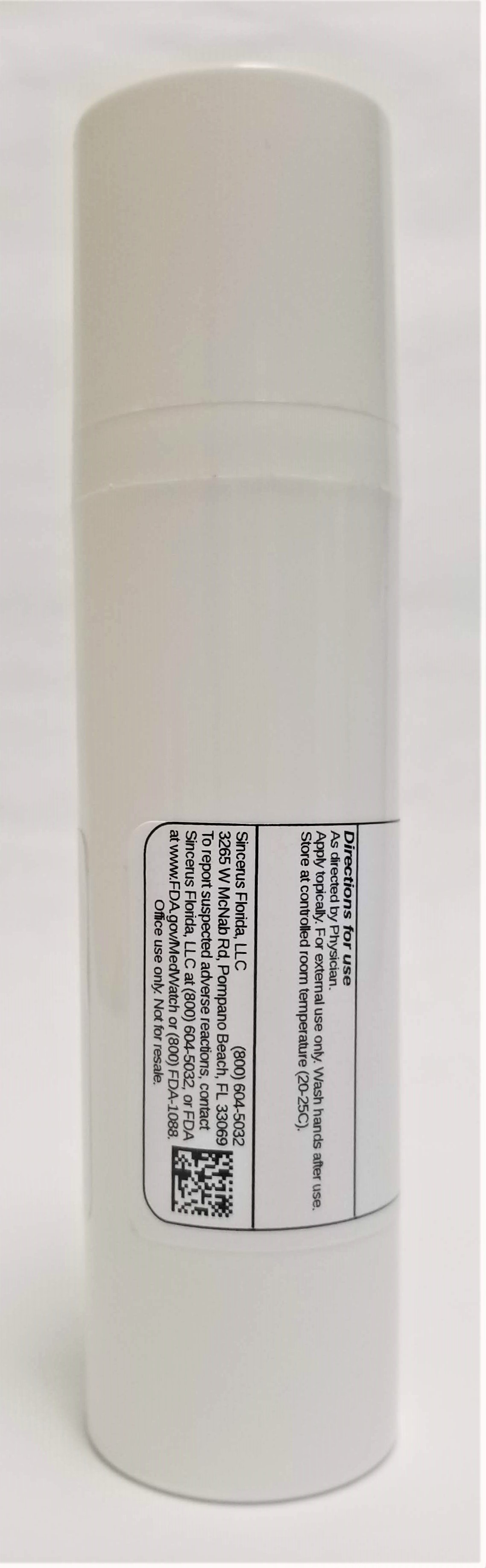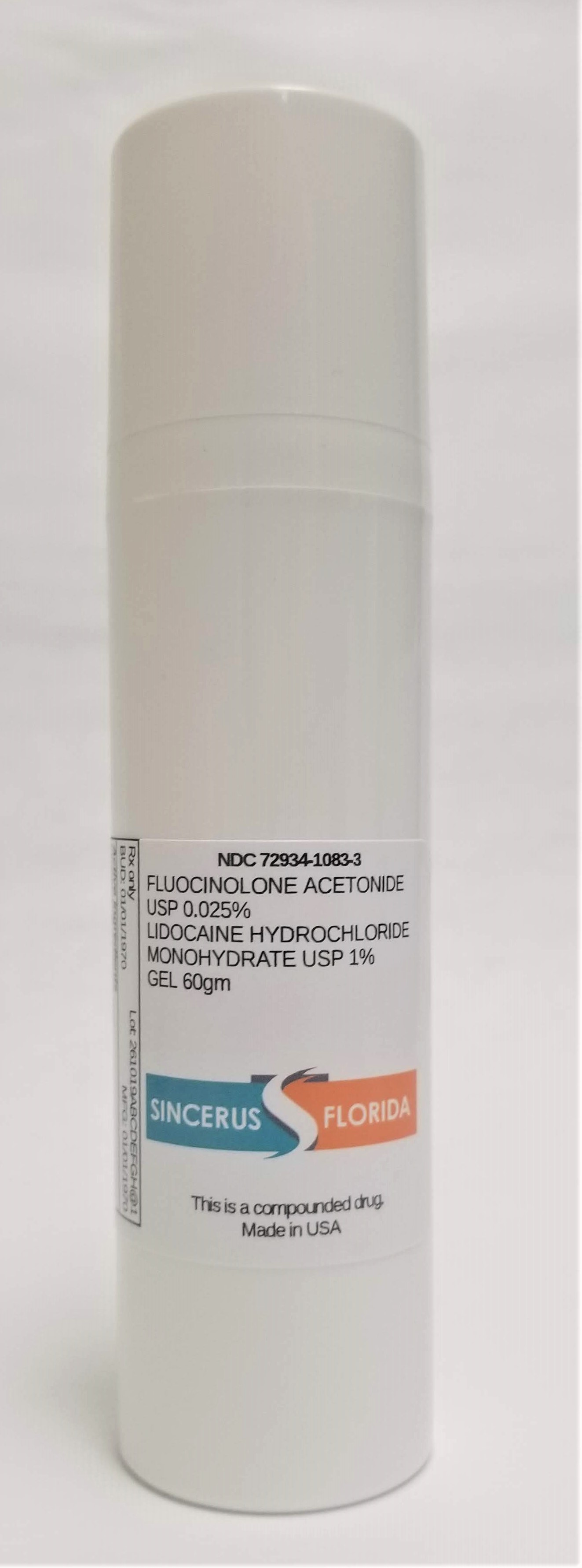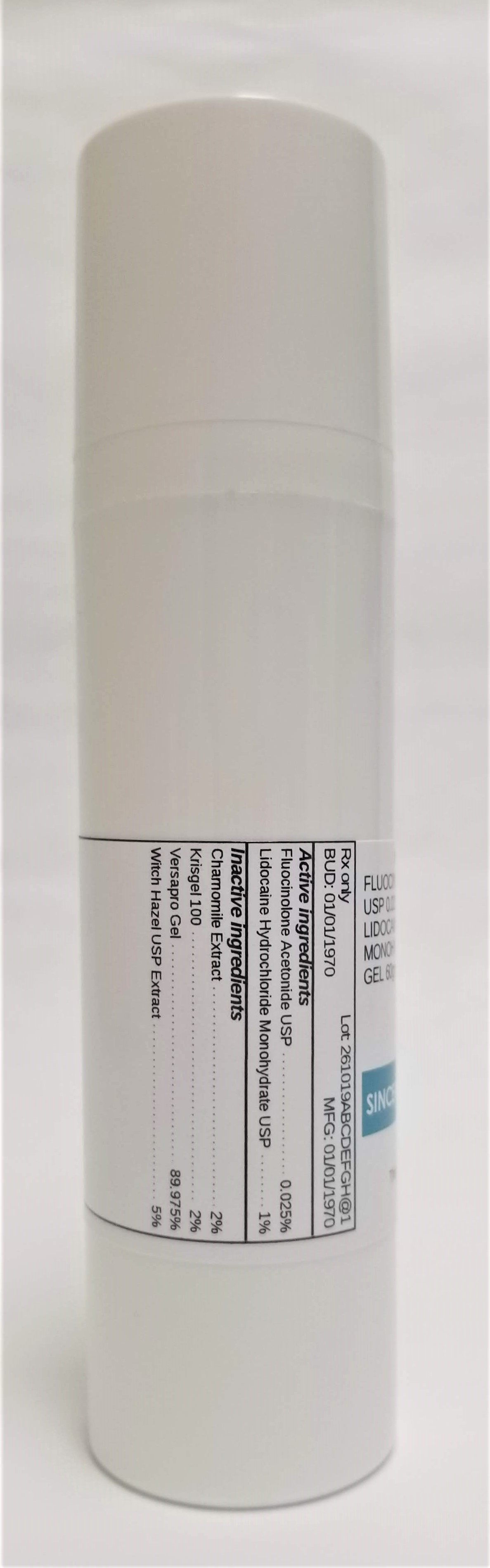 DRUG LABEL: FLUOCINOLONE ACETONIDE 0.025% / LIDOCAINE HCL MONOHYDRATE 1%
NDC: 72934-1083 | Form: GEL
Manufacturer: Sincerus Florida, LLC
Category: prescription | Type: HUMAN PRESCRIPTION DRUG LABEL
Date: 20190520

ACTIVE INGREDIENTS: LIDOCAINE HYDROCHLORIDE 1 g/100 g; FLUOCINOLONE ACETONIDE 0.025 g/100 g

FLUOCINOLONE ACETONIDE 0.025% / LIDOCAINE HCL MONOHYDRATE 1%